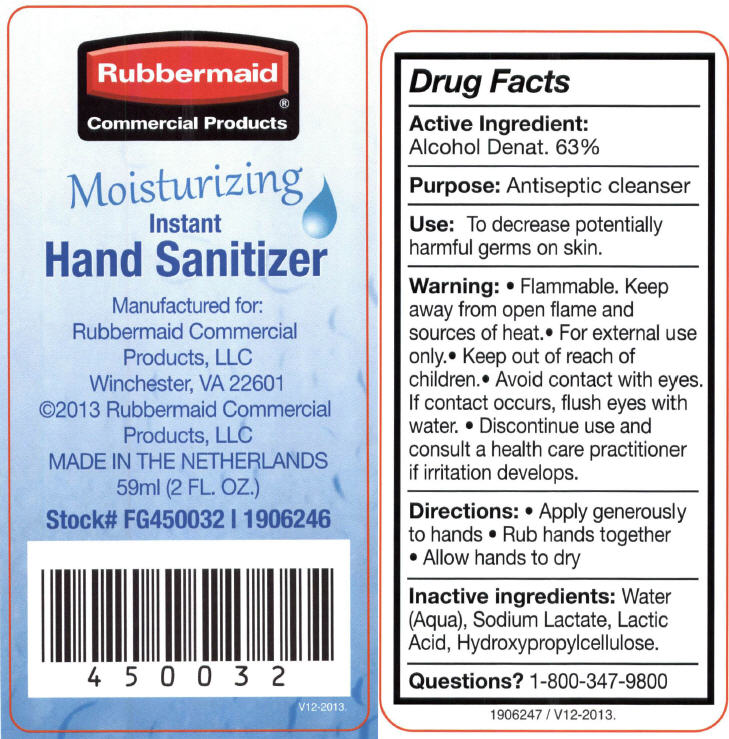 DRUG LABEL: Moisturizing Instant Hand Sanitizer
NDC: 65321-011 | Form: LIQUID
Manufacturer: Rubbermaid Commercial Products LLC
Category: otc | Type: HUMAN OTC DRUG LABEL
Date: 20240927

ACTIVE INGREDIENTS: ALCOHOL 63 mL/100 mL
INACTIVE INGREDIENTS: WATER; SODIUM LACTATE; LACTIC ACID, UNSPECIFIED FORM; HYDROXYPROPYL CELLULOSE (1600000 WAMW)

Moisturizing Instant Hand Sanitizer

Drug Facts

Active Ingredient

Alcohol Denat. 63%

Purpose

Antiseptic cleanser

Use

To decrease potentially harmful germs on skin.

Warning

- Flammable. Keep away from open flame and sources of heat.
- For external use only.

- Keep out of reach of children.
- Avoid contact with eyes. If contact occurs, flush eyes with water.
- Discontinue use and consult a health care practitioner if irritation develops.

Directions

- Apply generously to hands
- Rub hands together
- Allow hands to dry

Inactive ingredients

Water (Aqua), Sodium Lactate, Lactic Acid, Hydroxypropylcellulose.

Questions?

1-800-347-9800

PRINCIPAL DISPLAY PANEL - 59 ml Bottle Label

Rubbermaid®
Commercial Products

Moisturizing

Instant
Hand Sanitizer

Manufactured for:
Rubbermaid Commercial
Products, LLC
Winchester, VA 22601
©2013 Rubbermaid Commercial
Products, LLC
MADE IN THE NETHERLANDS
59ml (2 FL. OZ.)

Stock# FG450032 I 1906246

V12-2013.